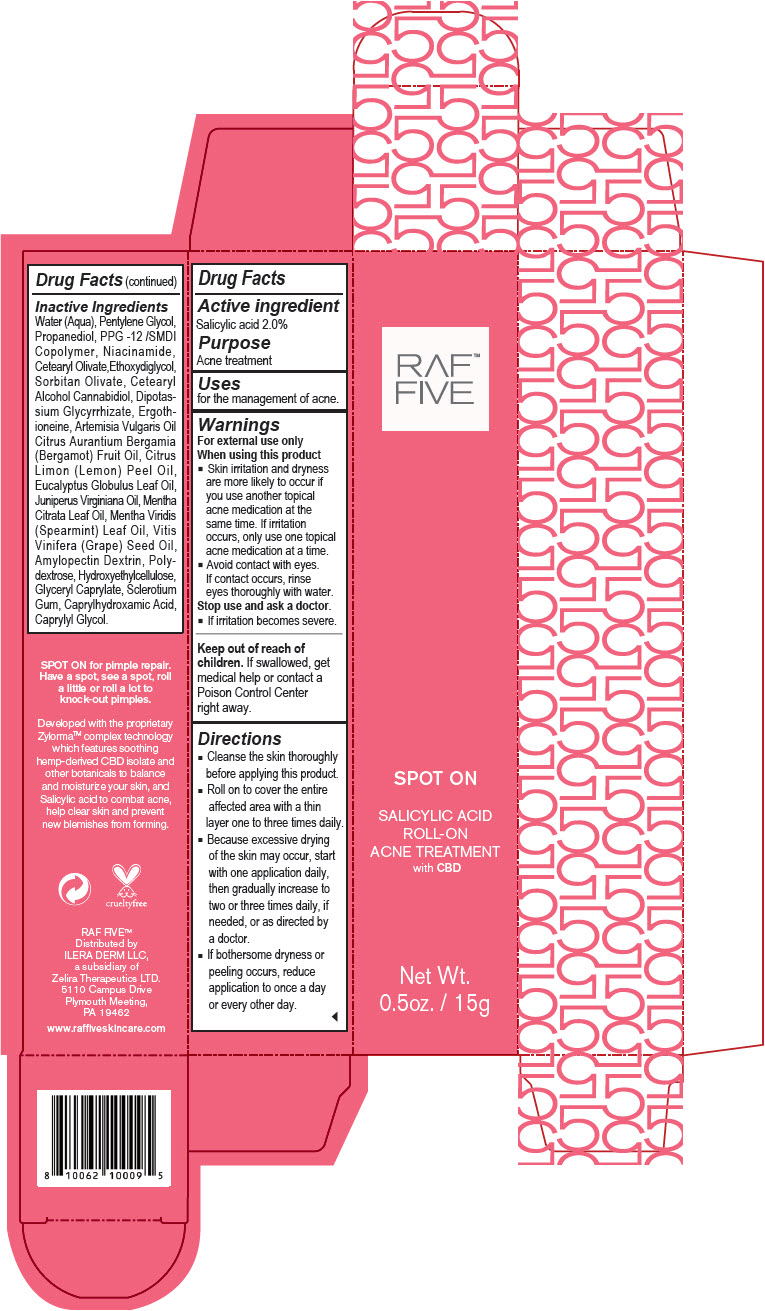 DRUG LABEL: RAF Five - Spot On Salicylic Acid Roll-On Acne Treatment
NDC: 66163-4455 | Form: CREAM
Manufacturer: Cosmetic Solutions LLC
Category: otc | Type: HUMAN OTC DRUG LABEL
Date: 20210826

ACTIVE INGREDIENTS: SALICYLIC ACID 2 g/100 g
INACTIVE INGREDIENTS: Water; Pentylene Glycol; Propanediol; PPG-12/SMDI Copolymer; Niacinamide; Cetearyl Olivate; Diethylene Glycol Monoethyl Ether; Sorbitan Olivate; Cetostearyl Alcohol; Cannabidiol; Glycyrrhizinate Dipotassium; Ergothioneine; Artemisia Vulgaris Top Oil; Bergamot Oil; Lemon Oil, Cold Pressed; Eucalyptus Oil; Juniperus Virginiana Oil; Spearmint Oil; Grape Seed Oil; Polydextrose; Hydroxyethyl Cellulose, Unspecified; Glyceryl Monocaprylate; Betasizofiran; Caprylhydroxamic Acid; Caprylyl Glycol

RAF™ Five - Spot On Salicylic Acid Roll-On Acne Treatment

Drug Facts

Active ingredient

Salicylic acid 2.0%

Purpose

Acne treatment

Uses

for the management of acne.

Warnings

For external use only

When using this product

- Skin irritation and dryness are more likely to occur if you use another topical acne medication at the same time. If irritation occurs, only use one topical acne medication at a time.
- Avoid contact with eyes. If contact occurs, rinse eyes thoroughly with water.

Stop use and ask a doctor.

- If irritation becomes severe.

Keep out of reach of children. If swallowed, get medical help or contact a Poison Control Center right away.

Directions

- Cleanse the skin thoroughly before applying this product.
- Roll on to cover the entire affected area with a thin layer one to three times daily.
- Because excessive drying of the skin may occur, start with one application daily, then gradually increase to two or three times daily, if needed, or as directed by a doctor.
- If bothersome dryness or peeling occurs, reduce application to once a day or every other day.

Inactive Ingredients

Water (Aqua), Pentylene Glycol, Propanediol, PPG -12 /SMDI Copolymer, Niacinamide, Cetearyl Olivate,Ethoxydiglycol, Sorbitan Olivate, Cetearyl Alcohol Cannabidiol, Dipotassium Glycyrrhizate, Ergothioneine, Artemisia Vulgaris Oil Citrus Aurantium Bergamia (Bergamot) Fruit Oil, Citrus Limon (Lemon) Peel Oil, Eucalyptus Globulus Leaf Oil, Juniperus Virginiana Oil, Mentha Citrata Leaf Oil, Mentha Viridis (Spearmint) Leaf Oil, Vitis Vinifera (Grape) Seed Oil, Amylopectin Dextrin, Polydextrose, Hydroxyethylcellulose, Glyceryl Caprylate, Sclerotium Gum, Caprylhydroxamic Acid, Caprylyl Glycol.

Distributed by
ILERA DERM LLC,
a subsidiary of
Zelira Therapeutics LTD.
5110 Campus Drive
Plymouth Meeting,
PA 19462

PRINCIPAL DISPLAY PANEL - 15 g Bottle Carton

RAF™
FIVE

SPOT ON

SALICYLIC ACID
ROLL-ON
ACNE TREATMENT
with CBD

Net Wt.
0.5oz. / 15g